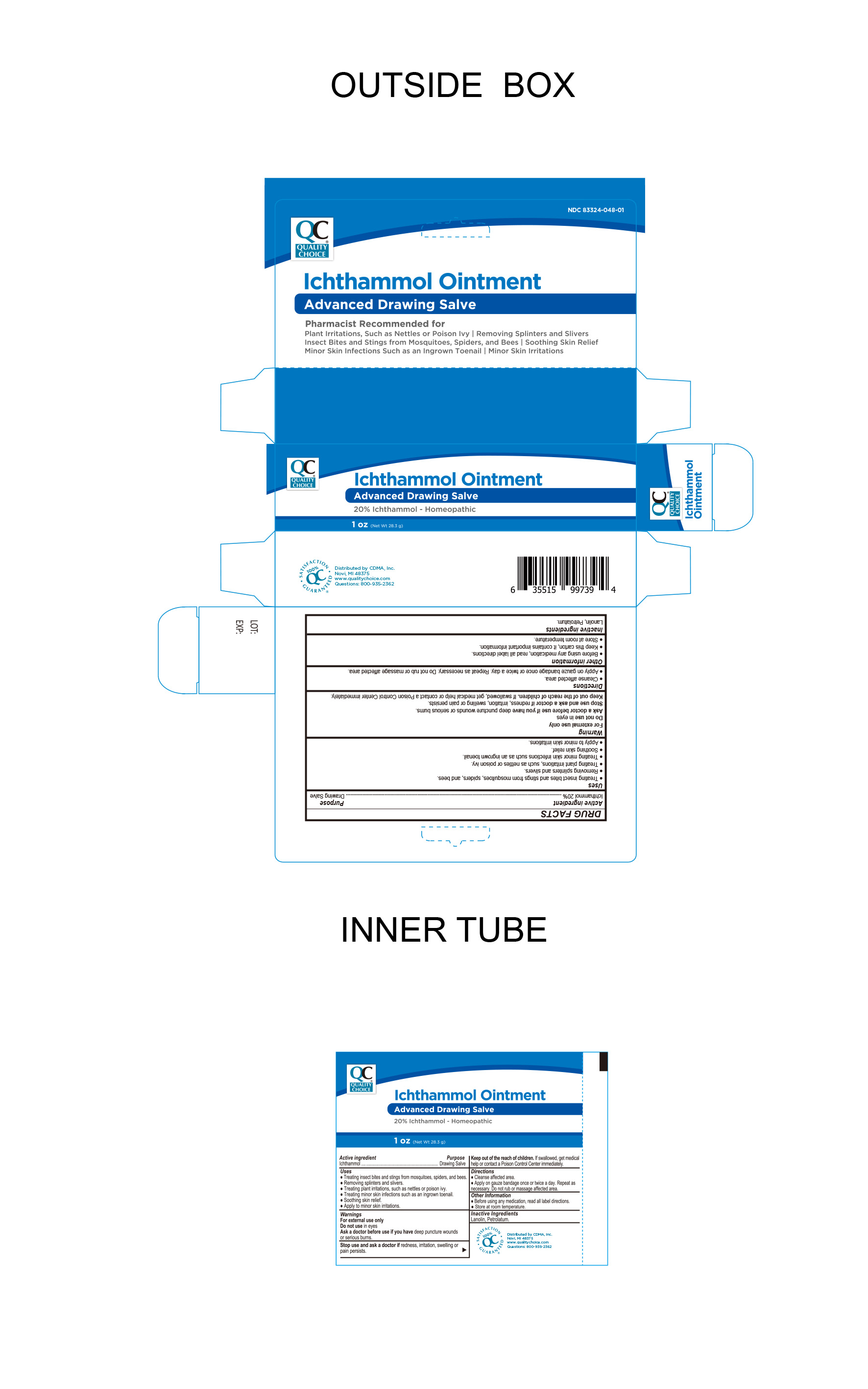 DRUG LABEL: Ichthammol 20%
NDC: 83324-048 | Form: OINTMENT
Manufacturer: Chain Drug Marketing Association, Inc.
Category: homeopathic | Type: HUMAN OTC DRUG LABEL
Date: 20240708

ACTIVE INGREDIENTS: ICHTHAMMOL 20 g/100 g
INACTIVE INGREDIENTS: PETROLATUM; LANOLIN

Quality Choice Ichthammol Ointment - Advanced Drawing Salve
20% Ichthammol - Homeopathic

Active ingredient

Ichthammol 20%

Purpose

Drawing Salve

Keep out of reach of children.

If swallowed, get medical help or contact a poison control center immediately.

Suggested Use

• Treating insect bites and stings from mosquitoes, spider, and bees • Removing splinters and silvers • Treating plant irritations, such as nettles or poison ivy • Treating minor skin infections such as an ingrown toenail • Soothing skin relief • Apply to minor skin irritations

Warnings

• For external use only • Do not use in eyes • Ask a doctor before use if you have deep puncture wounds or serious burns •

Directions

Cleanse affected area. Apply on gauze bandage once or twice a day. Repeat as necessary. Do not rub or massage affected area.

Stop use and ask a doctor if redness , irritation, swelling or pain persists.

Inactive Ingredients

Lanolin, Petrolatum

Distributed by CDMA., Inc.©

Novi, MI 48375

www.qualitychoice.com

Questions: 800-935-2362

Other Information

Before using any medication, read all label directions

Store at room temperature